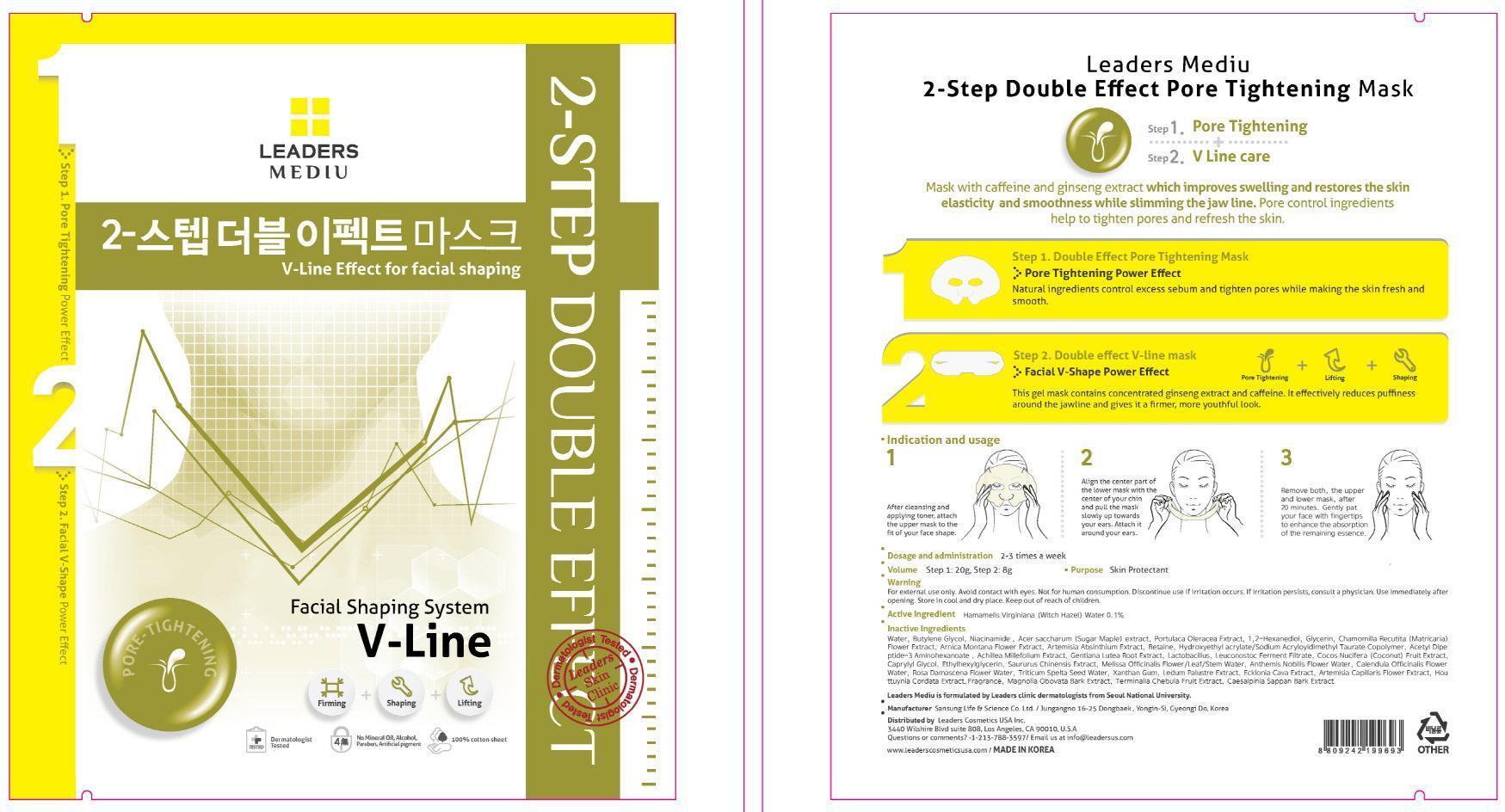 DRUG LABEL: Leaders Mediu 2 Step Double Effect Pore Tightening Mask
NDC: 69424-170 | Form: PATCH
Manufacturer: SANSUNG LIFE & SCIENCE CO., LTD.
Category: otc | Type: HUMAN OTC DRUG LABEL
Date: 20150410

ACTIVE INGREDIENTS: Witch Hazel 0.028 g/28 g
INACTIVE INGREDIENTS: Water; Butylene Glycol

ACTIVE INGREDIENT

Active Ingredient: Hamamelis Virginiana (Witch Hazel) Water 0.1%

INACTIVE INGREDIENT

Inactive Ingredients: Water, Butylene Glycol, Niacinamide , Acer saccharum (Sugar Maple) extract, Portulaca Oleracea Extract 1,2-Hexanediol, Glycerin, Chamomilla Recutita (Matricaria) Flower Extract, Arnica Montana Flower Extract, Artemisia Absinthium Extract, Betaine, Hydroxyethyl acrylate/Sodium Acryloyldimethyl Taurate Copolymer, Acetyl Dipeptide-3 Aminohexanoate , Achillea Millefolium Extract, Gentiana Lutea Root Extract, Lactobacillus, Leuconostoc Ferment Filtrate, Cocos Nucifera (Coconut) Fruit Extract, Caprylyl Glycol, Ethylhexylglycerin, Saururus Chinensis Extract, Melissa Officinalis Flower/Leaf/Stem Water, Anthemis Nobilis Flower Water, Calendula Officinalis Flower Water, Rosa Damascena Flower Water, Triticum Spelta Seed Water, Xanthan Gum, Ledum Palustre Extract, Ecklonia Cava Extract, Artemisia Capillaris Flower Extract, Houttuynia Cordata Extract,Fragrance, Magnolia Obovata Bark Extract, Terminalia Chebula Fruit Extract, Caesalpinia Sappan Bark Extract.

PURPOSE

Purpose: Skin Protectant

WARNINGS

Warning: For external use only. Avoid contact with eyes. Not for human consumption. Discontinue use if irritation occurs. If irritation persists, consult a physician. Use immediately after opening. Store in cool and dry place. Keep out of reach of children.

KEEP OUT OF REACH OF CHILDREN

INDICATIONS & USAGE

Indication and usage: 1. After cleansing and applying toner, attached the upper mask to fit your face shape. 2. Align the center part of the lower mask with the center of your chin and pull the mask up slowly towards your ears. Attached around the ears. 3. Leave on for about 20 minutes and remove both the upper and lower masks. Gently pat your face with fingertips to help the remaining essence to completely absorb into your skin.

DOSAGE & ADMINISTRATION

Dosage and administration: 2-3 times a week.